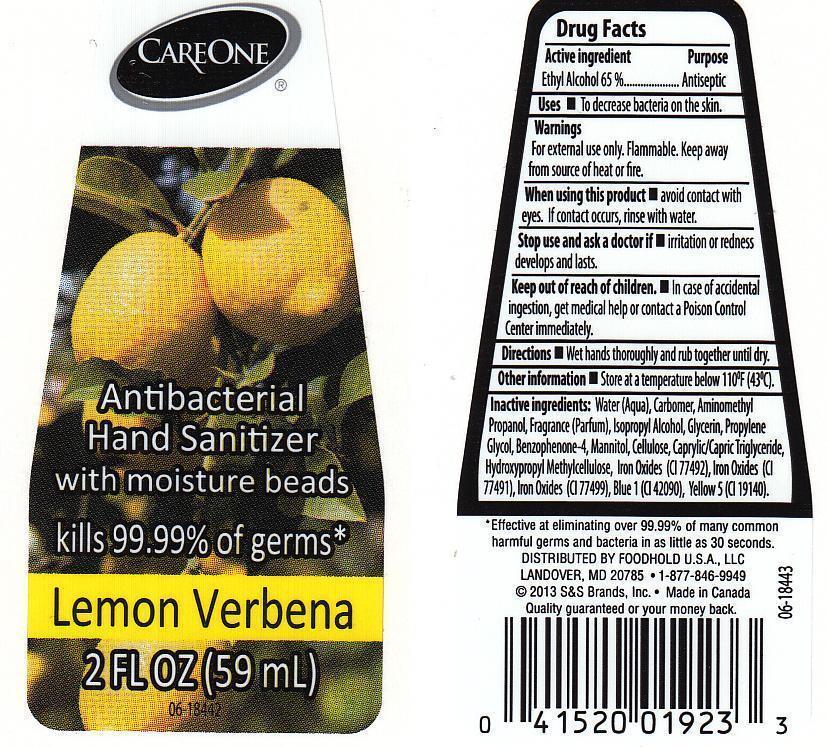 DRUG LABEL: CARE ONE
NDC: 41520-479 | Form: LIQUID
Manufacturer: AMERICAN SALES COMPANY
Category: otc | Type: HUMAN OTC DRUG LABEL
Date: 20130214

ACTIVE INGREDIENTS: ALCOHOL 650 mg/1 mL
INACTIVE INGREDIENTS: WATER; CARBOMER 934; AMINOMETHYLPROPANOL; ISOPROPYL ALCOHOL; GLYCERIN; PROPYLENE GLYCOL; SULISOBENZONE; MANNITOL; POWDERED CELLULOSE; MEDIUM-CHAIN TRIGLYCERIDES; HYPROMELLOSES; FERRIC OXIDE YELLOW; FERRIC OXIDE RED; FERROSOFERRIC OXIDE; FD&C BLUE NO. 1; FD&C YELLOW NO. 5

DRUG FACTS

ACTIVE INGREDIENT

ETHYL ALCOHOL 65%

PURPOSE

ANTISEPTIC

USES

TO DECREASE BACTERIA ON THE SKIN.

WARNINGS

FOR EXTERNAL USE ONLY. FLAMMABLE. kEEP AWAY FROM SOURCE OF HEAT OR FIRE.

WHEN USING THIS PRODUCT

AVOID CONTACT WITH EYES. IF CONTACT OCCURS, RINSE WITH WATER.

STOP USE AND ASK A DOCTOR IF

IRRITATION OR REDNESS DEVELOPS AND LASTS.

KEEP OUT OF REACH OF CHILDREN

IN CASE OF ACCIDENTAL INGESTION, GET MEDICAL HELP OR CONTACT A POISON CONTROL CENTER IMMEDIATELY.

DIRECTIONS

WET HANDS THOROUGHLY AND RUN TOGETHER UNTIL DRY.

OTHER INFORMATION

STORE AT A TEMPERTAURE BELOW 110F (43C)

INACTIVE INGREDIENTS:

WATER (AQUA), CARBOMER, AMINOMETHYL PROPANOL, FRAGRANCE (PARFUM), ISOPROPYL ALCOHOL, GLYCERIN, PROPYLENE GLYCOL, BENZOPHENONE-4, MANNITOL, CELLULOSE, CAPRYLIC/CAPRIC TRIGLYCERIDE, HYDROXYPROPYL METHYLCELLULOSE, IRON OXIDES (CI 77492), IRON OXIDES (CI 77491), IRON OXIDES (CI 77499), BLUE 1 (CI 42090), YELLOW 5 (CI 19140).